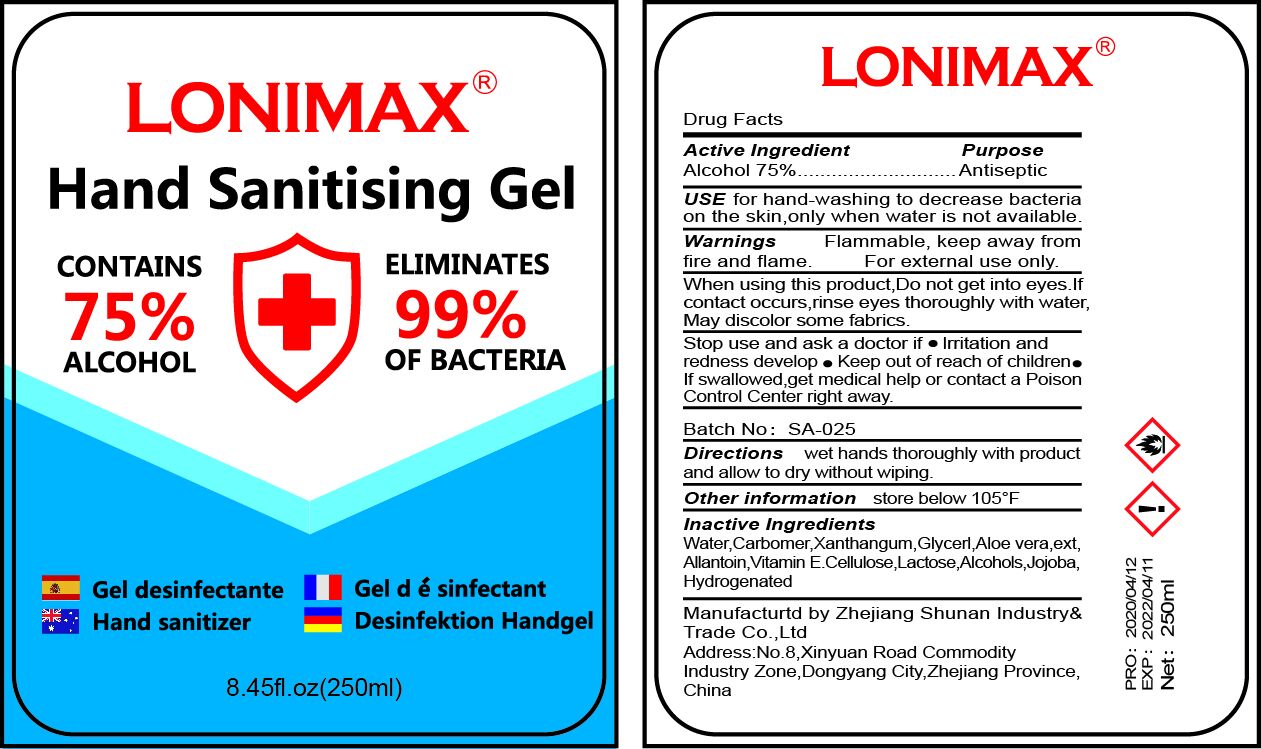 DRUG LABEL: LONIMAX Hand Sanitising
NDC: 75556-001 | Form: GEL
Manufacturer: ZHEJIANG SHUNAN INDUSTRY&TRADE CO., LTD
Category: otc | Type: HUMAN OTC DRUG LABEL
Date: 20200502

ACTIVE INGREDIENTS: ALCOHOL 75 mL/100 mL
INACTIVE INGREDIENTS: GLYCERIN; XANTHAN GUM; WATER; CARBOMER 934; TOCOPHEROL; ALOE VERA WHOLE; ALLANTOIN; ALPHA CELLULOSE; .ALPHA.-LACTOSE; HYDROGENATED JOJOBA OIL

NA

Active Ingredient(s)

Alcohol 75%

Purpose

Antiseptic

Use

For hand washing to help decrease bacteria on the skin only when water is not available

Warnings

For external use only. Flammable. Keep away from fire and flame

When using this product do not get into eyes. When contact occurs, rinse eyes thoroughly with water

May discolor fabrics

Stop use and ask a doctor if irritation and redness develop

Keep out of reach of children. If swallowed, get medical help or contact a Poison Control Center right away.

Directions

- Wet hands thoroughly with product and allow to dry without wiping

Other information

- Store below 105F

Inactive ingredients

Water, Carbomer, Xanthan Gum, glycerin, Aloe Vera Extract, Allantoin, Vitamin E, Cellulose, Lactose, Jojoba Alcohol, Hyfrogenated